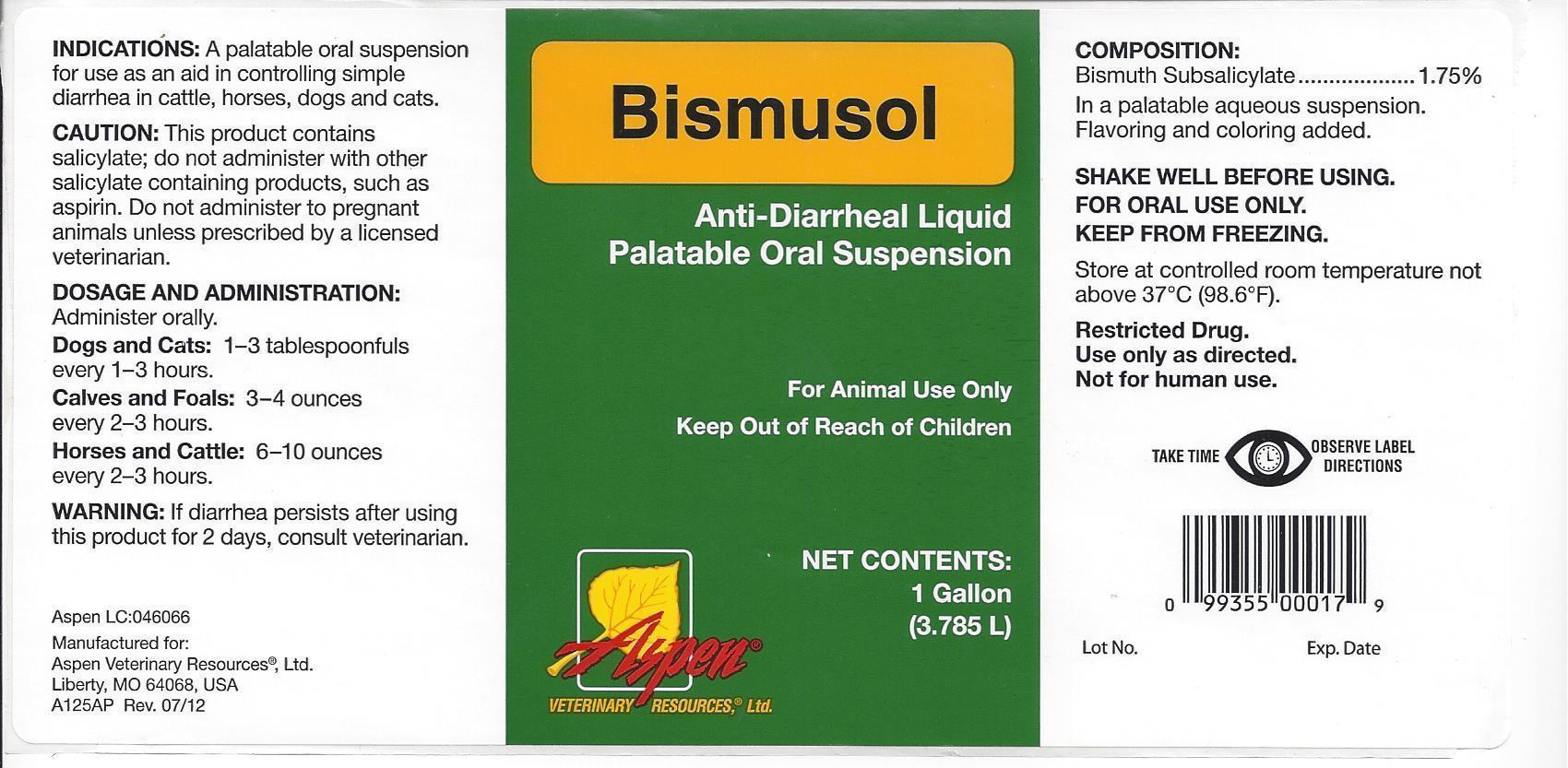 DRUG LABEL: Bismuth
NDC: 46066-002 | Form: SUSPENSION
Manufacturer: ASPEN VETERINARY
Category: animal | Type: OTC ANIMAL DRUG LABEL
Date: 20130918

ACTIVE INGREDIENTS: BISMUTH SUBSALICYLATE 18 mg/1 mL
INACTIVE INGREDIENTS: GUAR GUM; POTASSIUM SORBATE; SACCHARIN SODIUM; METHYL SALICYLATE; WATER; D&C RED NO. 33; SILICON DIOXIDE

ASPEN VETERINARY BISMUSOL

BISMUSOL

Anti-Diarrheal Liquid

Palatable Oral Suspension

For Animal Use Only

Keep Out of Reach of Children

NET CONTENTS:

1 Gallon

(3.785 L)

ASPEN

Veterinary Resources, Ltd.

INDICATIONS:

A palatable oral suspension for use as an aid in controlling simple diarrhea in cattle, horses, dogs and cats.

CAUTION:

This product contains salicylate; do not administer with other salicylate-containing products, such as aspirin. Do not administer to pregnant animals unless prescribed by a licensed veterinarian.

DOSAGE AND ADMINISTRATION:

Administer orally.

Dogs and Cats: 1 - 3 tablespoonfuls every 1-3 hours

Calves and Foals: 3 - 4 ounces every 2-3 hours

Cattle and Horses: 6 - 10 ounces every 2-3 hours

WARNING:

If diarrhea persists after using this product for 2 days, contact a veterinarian.

Aspen LC:046066

Manufactured for:

Aspen Veterinary Resources, Ltd.

Liberty, MO 64068, USA

A125AP Rev. 07/12

COMPOSITION:

Bismuth Subsalicylate..........1.75%

In a palatable aqueous suspension.

Flavoring and coloring added.

SHAKE WELL BEFORE USING. FOR ORAL USE ONLY. KEEP FROM FREEZING.

Store at controlled room temperature not above 37ºC (98.6ºF).

Restricted Drug.

Use only as directed.

Not for human use.

TAKE TIME OBSERVE LABEL DIRECTIONS

Lot No. Exp. Date